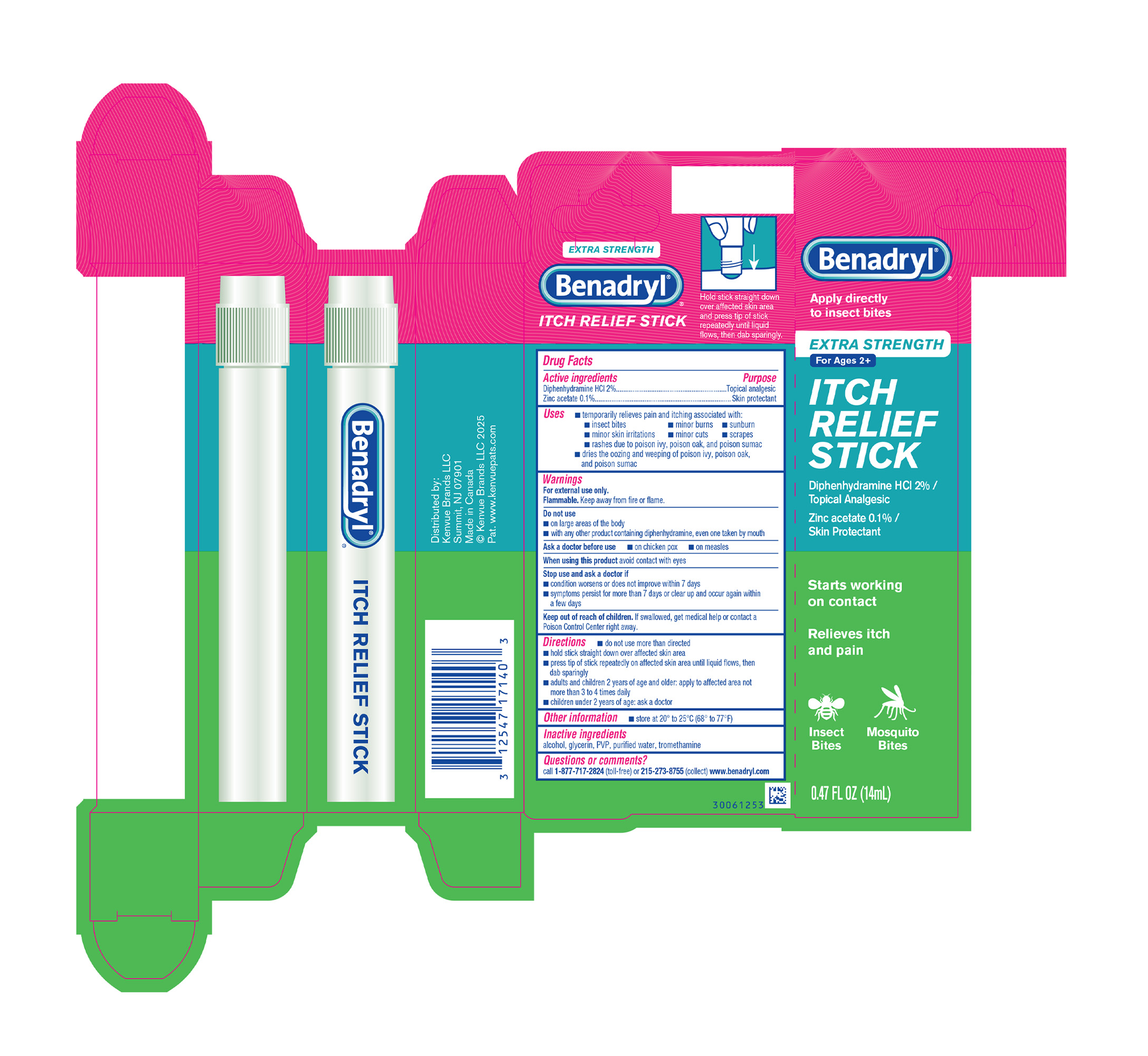 DRUG LABEL: Benadryl Extra Strength Itch Relief
NDC: 69968-0459 | Form: SOLUTION
Manufacturer: Kenvue Brands LLC
Category: otc | Type: HUMAN OTC DRUG LABEL
Date: 20250710

ACTIVE INGREDIENTS: ZINC ACETATE 1 mg/1 mL; DIPHENHYDRAMINE HYDROCHLORIDE 20 mg/1 mL
INACTIVE INGREDIENTS: ALCOHOL; WATER; POVIDONE, UNSPECIFIED; GLYCERIN; TROMETHAMINE

Benadryl® EXTRA STRENGTH ITCH RELIEF STICK

Drug Facts

ACTIVE INGREDIENT

Active ingredient | Purpose
Diphenhydramine HCl 2% | Topical analgesic
Zinc acetate 0.1% | Skin protectant

Uses

- temporarily relieves pain and itching associated with:
  - insect bites
  - minor burns
  - sunburn
  - minor skin irritations
  - minor cuts
  - scrapes
  - rashes due to poison ivy, poison oak, and poison sumac
  - dries the oozing and weeping of poison ivy, poison oak and poison sumac

Warnings

For external use only.

Flammable. Keep away from fire or flame.

Do not use

- on large areas of the body
- with any other product containing diphenhydramine, even one taken by mouth

Ask a doctor before use

- on chicken pox
- on measles

When using this product avoid contact with eyes

Stop use and ask a doctor if

- condition worsens or does not improve within 7 days
- symptoms persist for more than 7 days or clear up and occur again within a few days

Keep out of reach of children. If swallowed, get medical help or contact a Poison Control Center right away.

Directions

- do not use more than directed
- hold stick straight down over affected skin area
- press tip of stick repeatedly on affected skin area until liquid flows, then dab sparingly
- adults and children 2 years of age and older: apply to affected area not more than 3 to 4 times daily
- children under 2 years of age: ask a doctor

Other information

- store at 20° to 25° C (68° to 77° F)

Inactive ingredients

alcohol, glycerin, PVP, purified water, tromethamine

Questions or comments?

call 1-877-717-2824 (toll-free) or 215-273-8755 (collect) www.benadryl.com

Distributed by:

Kenvue Brands LLC
Summit, NJ 07901

PRINCIPAL DISPLAY PANEL - 14 mL Applicator Carton

Benadryl®®

Apply directly

to insect bites

EXTRA STRENGTH

For Ages 2+

ITCH

RELIEF

STICK

Diphenhydramine HCL 2% /

Topical Analgesic

Zinc acetate 0.1% /

Skin Protectant

Starts working

on contact

Relieves itch

and pain

Insect Mosquito

Bites Bites

0.47 FL OZ (14mL)